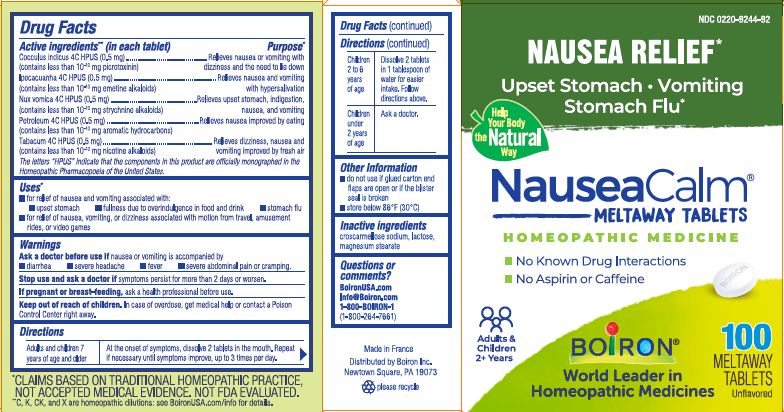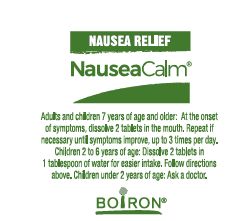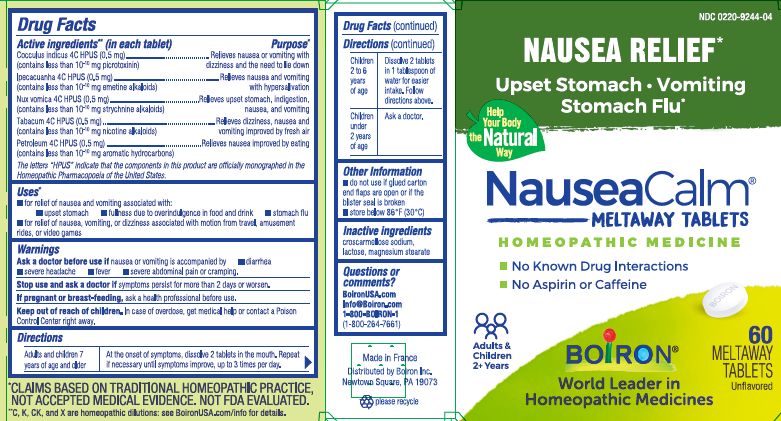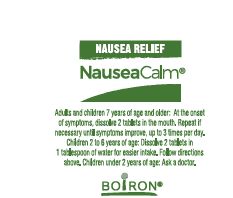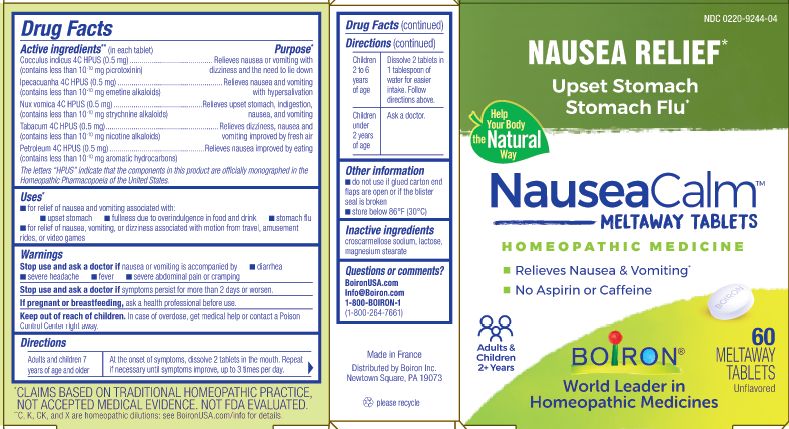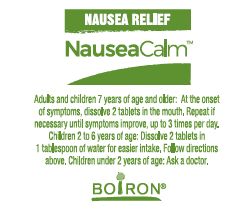 DRUG LABEL: NauseaCalm
NDC: 0220-9244 | Form: TABLET
Manufacturer: Boiron
Category: homeopathic | Type: HUMAN OTC DRUG LABEL
Date: 20250321

ACTIVE INGREDIENTS: ANAMIRTA COCCULUS SEED 4 [hp_C]/1 1; KEROSENE 4 [hp_C]/1 1; TOBACCO LEAF 4 [hp_C]/1 1; IPECAC 4 [hp_C]/1 1; STRYCHNOS NUX-VOMICA SEED 4 [hp_C]/1 1
INACTIVE INGREDIENTS: LACTOSE, UNSPECIFIED FORM; MAGNESIUM STEARATE; CROSCARMELLOSE SODIUM

NauseaCalm Tablets

Active ingredient** (in each tablet)

Cocculus indicus 4C HPUS (0.5 mg) (contains less than 10^-10 mg picrotoxinin)

Ipecacuanha 4C HPUS (0.5 mg) (contains less than 10^-10 mg emetine alkaloids)

Nux Vomica 4C HPUS (0.5 mg) (contains less than 10^-10 strychnine alkaloids)

Petroleum 4C HPUS (0.5 mg) (contains less than 10^-10 aromatic hydrocarbons)

Tabacum 4C HPUS (0.5 mg) (contains less than 10^-10 nicotine alkaloids)

The letters "HPUS" indicate that the components in this product are officially monographed in the Homeopathic Pharmacopoeia of the United States.

Purpose*

Cocculus indicus 4C HPUS ... Relieves nausea or vomiting with dizziness and the need to lie down

Ipecacuanha 4C HPUS ... Relieves nausea and vomiting with hypersalivation

Nux Vomica 4C HPUS ... Relieves upset stomach, indigestion, nausea, and vomiting

Petroleum 4C HPUS ... Relieves nausea improved by eating

Tabacum 4C HPUS ... Relieves dizziness, nausea and vomiting improved by fresh air

Uses*

- for relief of nausea and vomiting associated with:

- upset stomach
- fullness due to overindulgence in food and drink
- stomach flu
- for relief of nausea, vomiting, or dizziness associated with motion from travel, amusement rides, or video games

Ask a doctor before useif nausea or vomiting is accompanied by

- diarrhea
- severe headache
- fever
- severe abdominal pain or cramping.

Stop use and ask a doctor if symptoms persist for more than 2 days or worsen.

PREGNANCY OR BREAST FEEDING

If pregnant or breast-feeding, ask a health professional before use.

Keep out of reach of children. In case of overdose, get medical help or contact a Poison Control Center right away.

Directions

Adults and children 7 years of age and older - At the onset of symptoms, dissolve 2 tablets in the mouth. Repeat if necessary until symptoms improve, up to 3 times per day.

Children 2 to 6 years of age - Dissolve 2 tablets in 1 tablespoon of water for easier intake. Follow directions above.

Children under 2 years of age - Ask a doctor.

INACTIVE INGREDIENT

croscarmellose sodium, lactose, magnesium stearate

do not use if glued carton end flaps are open or if the blister seal is broken

store below 86° F (30° C)

Nausea Relief*

No Aspirin or Caffeine

60 Meltaway Tablets unflavored

100 Meltaway Tablets unflavored

No Known Drug Interactions

*CLAIMS BASED ON TRADITIONAL HOMEOPATHIC PRACTICE, NOT ACCEPTED MEDICAL EVIDENCE. NOT FDA EVALUATED.
**C,K,CK, and X are homeopathic dilutions: see BoironUSA.com/info for details.

Questions or Comments?

BoironUSA.com

Info@Boiron.com

1-800-BOIRON-1

(1-800-264-7661)

Made if France

Distributed by Boiron Inc.

Newtown Square, PA 19073